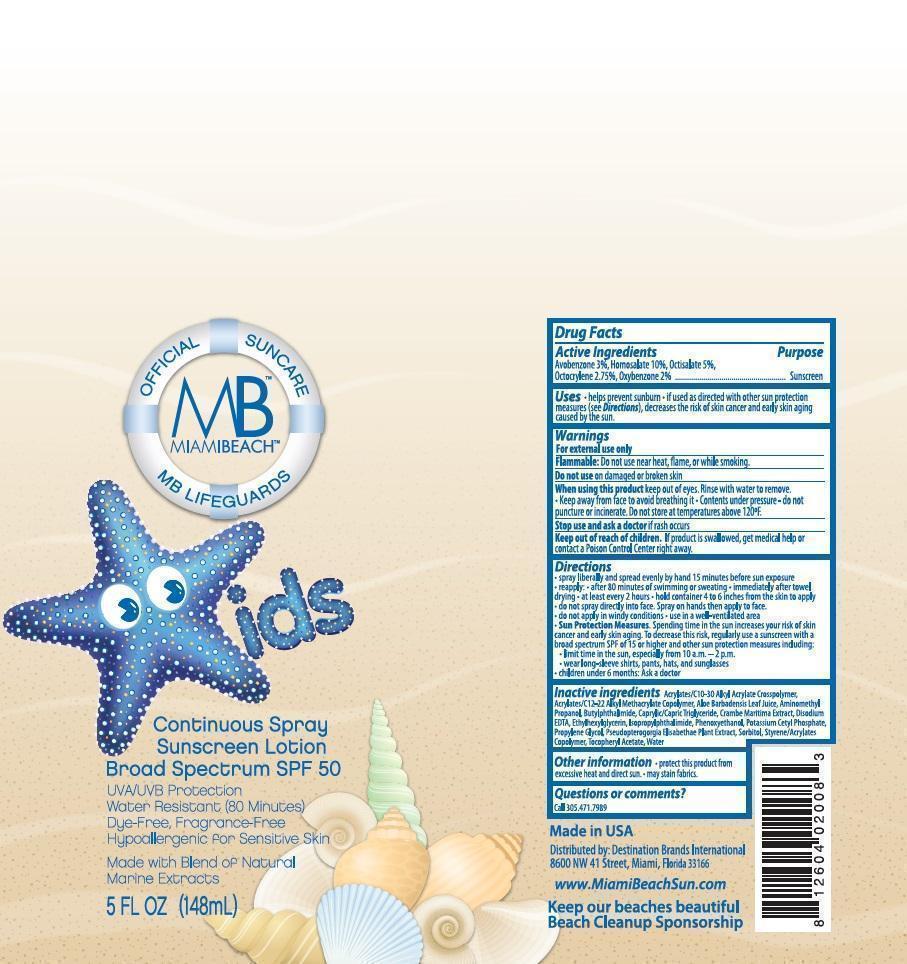 DRUG LABEL: BLI Holding
NDC: 13630-0074 | Form: AEROSOL, SPRAY
Manufacturer: Prime Packaging, Inc.
Category: otc | Type: HUMAN OTC DRUG LABEL
Date: 20200117

ACTIVE INGREDIENTS: AVOBENZONE 30.33 mg/1 mL; HOMOSALATE 101.1 mg/1 mL; OCTISALATE 50.55 mg/1 mL; OCTOCRYLENE 27.8025 mg/1 mL; OXYBENZONE 20.22 mg/1 mL
INACTIVE INGREDIENTS: (C10-C30)ALKYL METHACRYLATE ESTER; BUTYL ACRYLATE/C16-C20 ALKYL METHACRYLATE/METHACRYLIC ACID/METHYL METHACRYLATE COPOLYMER; ALOE VERA LEAF; AMINOMETHYLPROPANOL; N-BUTYLPHTHALIMIDE; ISOPROPYLPHTHALIMIDE; EDETATE DISODIUM; PHENOXYETHANOL; ETHYLHEXYLGLYCERIN; POTASSIUM CETYL PHOSPHATE; PROPYLENE GLYCOL; WATER; PSEUDOPTEROGORGIA ELISABETHAE; CAPRYLIC/CAPRIC ACID; CRAMBE MARITIMA LEAF; SORBITOL; STYRENE/ACRYLAMIDE COPOLYMER (MW 500000); ALPHA-TOCOPHEROL ACETATE

Active ingredients

Avobenzone 3 %, Homosalate 10 %, Octisalate 5 %, Octocrylene 2.75 %, and Oxybenzone 2 %

Purpose

Sunscreen

Uses

- helps prevent sunburn
- if used as directed with other sun protection measures (see Directions), decreases the risk of skin cancer and early skin aging caused by the sun

Warnings

OTHER SAFETY INFORMATION

For external use only

DO NOT USE

Flammable: Do not use near heat, flame, or while smoking.

Do not use on damaged or broken skin

When using this product keep out of eyes. Rinse with water to remove. •Keep away from face to avoid breathing it. •Contents under pressure-do not puncture or incinerate. Do not store at temperatures above 120°F

Stop use and ask a doctor if rash occurs

Keep out of reach of children. If product is swallowed, get medical help or contact a Poison Control Center right away.

Directions

- spray liberally and spread evenly by hand 15 minutes before sun exposure
- reapply: •after 80 minutes of swimming or sweating •immediately after towel drying •at least every 2 hours •hold container 4 to 6 inches from the skin to apply
- do not spray directly into face. Spray on hands then apply to face.
- do not apply in windy conditions •use in a well-ventilated area
- Sun Protection Measures. Spending time in the sun increases your risk of skin cancer and early skin aging. To decrease this risk, regularly use a sunscreen with a broad spectrum SPF of 15 or higher and other sun protection measures including:
  - limit time in the sun, especially from 10 a.m. – 2 p.m.
  - wear long-sleeve shirts, pants, hats, and sunglasses
- children under 6 months: Ask a doctor

Inactive Ingredients

Acrylates/C10-30 Alkyl Acrylate Crosspolymer, Acrylates/C12-22 Alkyl Methacrylane Copolymerm, Aloe Barbadensis Leaf Juice, Aminomethyl Propanol, Butylphthalimide,Capylic/Capric Triglyceride, Crambe Maritima Extract, Disodium EDTA, Ethylhexylglycerin, Isopropylphthalimide, Phenoxyethanol, Potassium Cetyl Phosphate, Propylene Glycol, Pseudopterogorgia Elisabethae Plant Extract, Sorbitol, Styrene/ Acrylates Copolymer, Tocophenyl Acetate, Water

Other Information

•protect this product from excessive heat and direct sun •may stain fabrics.

Questions or comments?

Call 305.471.7989

PRINCIPAL DISPLAY PANEL - 148 mL Can Label

OFFICIAL SUNCARE

MB

MIAMIBEACH

MB LIFEGUARDS

KIDS

CONTINUOUS SPRAY

SUNSCREEN LOTION

BROAD SPECTRUM SPF 50

UVA/UVB Protection

Water Resistant (80 Minutes)

Dye-Free, Fragrance-Free

Hypoallergenic for Sensitive Skin

Made with Blend of Natural Marine Extracts

5 FL OZ (148mL)